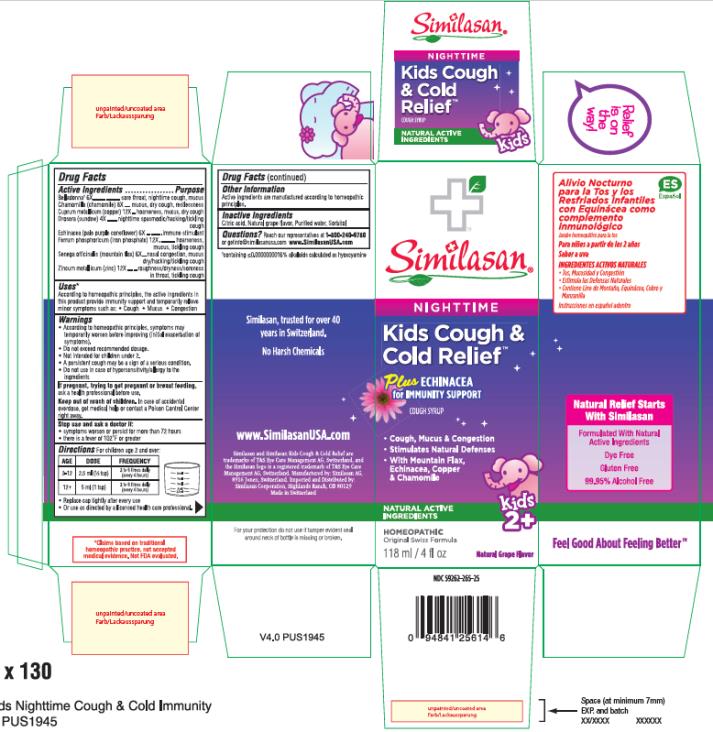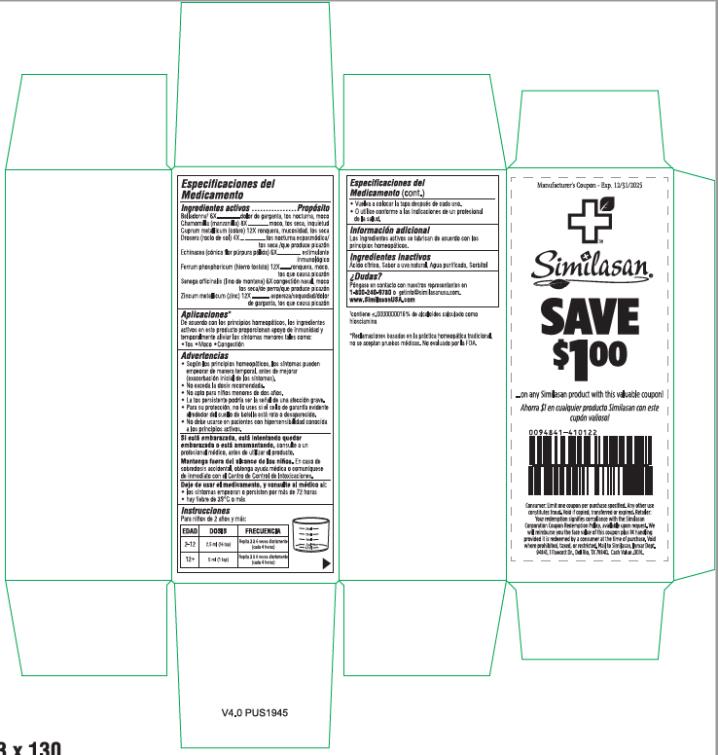 DRUG LABEL: Kids Cough and Cold Relief Plus Echinacea, Nighttime
NDC: 59262-265 | Form: SYRUP
Manufacturer: Similasan Corporation
Category: homeopathic | Type: HUMAN OTC DRUG LABEL
Date: 20230111

ACTIVE INGREDIENTS: ATROPA BELLADONNA 6 [hp_X]/1 mL; MATRICARIA RECUTITA 8 [hp_X]/1 mL; COPPER 12 [hp_X]/1 mL; DROSERA ROTUNDIFOLIA FLOWERING TOP 4 [hp_X]/1 mL; ECHINACEA PALLIDA 6 [hp_X]/1 mL; FERROSOFERRIC PHOSPHATE 12 [hp_X]/1 mL; POLYGALA SENEGA ROOT 6 [hp_X]/1 mL; ZINC 12 [hp_X]/1 mL
INACTIVE INGREDIENTS: CITRIC ACID MONOHYDRATE; WATER; SORBITOL

Kids Cough and Cold Relief Plus Echinacea, Nighttime

Drug Facts

Active Ingredient

Belladonna* 6X

Purpose

sore throat, nighttime cough, mucus

Active Ingredient

Chamomilla (chamomile) 8X

Purpose

mucus, dry cough, restlessness

Active Ingredient

Cuprum metallicum (copper) 12X

Purpose

hoarseness, mucus, dry cough

Active Ingredient

Drosera (sundew) 4X

Purpose

nighttime spasmodic/hacking/tickling cough

Active Ingredient

Echinacea (pale purple coneflower) 6X

Purpose

immune stimulant

Active Ingredient

Ferrum phosphoricum (iron phosphate) 12X

Purpose

hoarseness, mucus, tickling cough

Active Ingredient

Senega officinalis (mountain flax) 6X

Purpose

nasal congestion, mucus, dry/hacking/tickling cough

Active Ingredient

Zincum metallicum (zinc) 12X

Purpose

Roughness/dryness/soreness in throat, tickling cough

Uses*

According to homeopathic principles, the active ingredients in this product provide immunity support and temporarily relieve minor symptoms such as:

- Cough
- Mucus
- Congestion

Warnings

- According to homeopathic principles, symptoms may temporarily worsen before improving (initial exacerbation of symptoms).
- Do not exceed recommended dosage.
- Not intended for children under 2.
- A persistent cough may be a sign of a serious condition.
- Do not use in case of hypersensitivity/allergy to the ingredients

If pregnant, trying to get pregnant or breast feeding,

ask a health professional before use.

Keep out of reach of children.

In case of accidental overdose, get medical help or contact a Poison Control Center right away.

Stop use and ask a doctor if

- symptoms worsen or persist for more than 72 hours
- there is a fever of 102°F or greater

Directions

For children age 2 and over:

AGE | DOSE | FREQUENCY
2-12 | 2.5 ml (½ tsp) | 3 to 6 times daily (every 4 hours)
12+ | 5 ml (1 tsp) | 3 to 6 times daily (every 4 hours)

- Replace cap tightly after every use
- Or use as directed by a licensed health care professional.

Other Information:

Active ingredients are manufactured according to homeopathic principles.

Inactive Ingredients:

Citric acid, Natural grape flavor, Purified water, Sorbitol

Questions? Reach our representatives at 1-800-240-9780 or getinfo@similasanusa.com www.SimilasanUSA.com

*containing ≤0.0000000016% alkaloids calculated as hyoscyamine

PRINCIPAL DISPLAY PANEL

Similasan®
NIGHTTIME

Kids Cough &
Cold Relief
Plus ECHINACEA
for IMMUNITY SUPPORT
COUGH SYRUP
118 ml / 4 fl oz